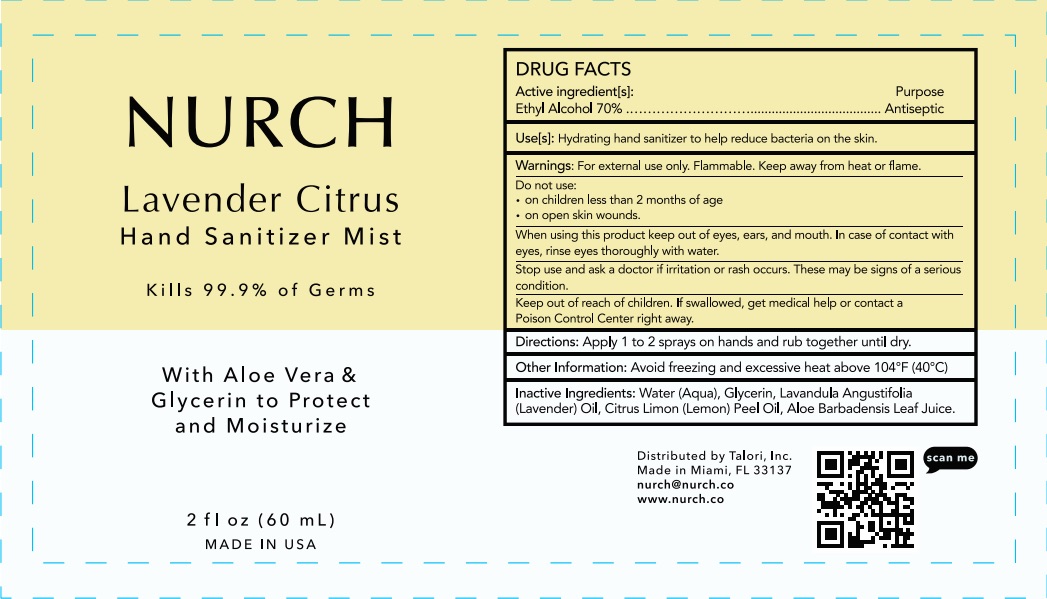 DRUG LABEL: NURCH
NDC: 79666-111 | Form: LIQUID
Manufacturer: Talori, Inc
Category: otc | Type: HUMAN OTC DRUG LABEL
Date: 20200718

ACTIVE INGREDIENTS: ALCOHOL 70 mL/100 mL
INACTIVE INGREDIENTS: GLYCERIN; LAVENDER OIL; WATER; LEMON OIL; ALOE VERA LEAF

NURCH Sanitizer Mist

Active Ingredient(s)

Alcohol 70% v/v. Purpose: Antiseptic

Purpose

Antiseptic, Hand Sanitizer

Use

Hydrating hand Sanitizer to help reduce bacteria on the skin.

Warnings

For external use only. Flammable. Keep away from heat or flame

Do not use

- in children less than 2 months of age
- on open skin wounds

When using this product keep out of eyes, ears, and mouth. In case of contact with eyes, rinse eyes thoroughly with water.
Stop use and ask a doctor if irritation or rash occurs. These may be signs of a serious condition.
Keep out of reach of children. If swallowed, get medical help or contact a Poison Control Center right away.

Stop use and ask a doctor if irritation or rash occurs. These may be signs of a serious condition.

Keep out of reach of children. If swallowed, get medical help or contact a Poison Control Center right away.

Directions

Apply 1 to 2 sprays on hand and rub together until dry.

Other information

- Avoid freezing and excessive heat above 104F (40C)

Inactive ingredients

aloe vera leaf juice, glycerin, lavender oil, lemon peel oil, water,

Package Label - Principal Display Panel

60 mL NDC: 79666-111-11